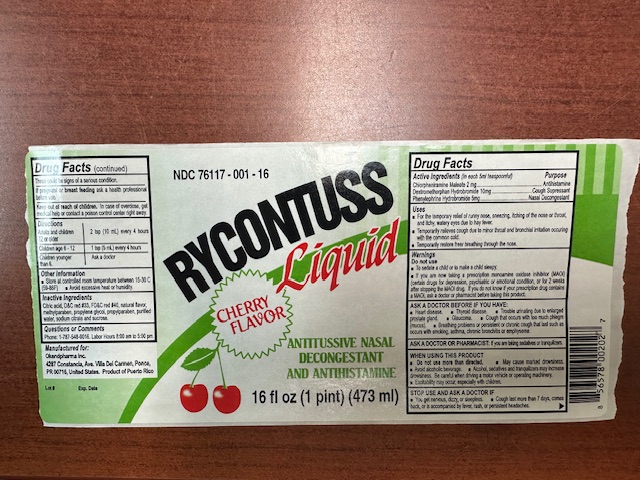 DRUG LABEL: Rycontuss
NDC: 65852-021 | Form: LIQUID
Manufacturer: Dextrum Laboratories, Inc
Category: otc | Type: HUMAN OTC DRUG LABEL
Date: 20251021

ACTIVE INGREDIENTS: PHENYLEPHRINE HYDROCHLORIDE 5 mg/5 mL; CHLORPHENIRAMINE MALEATE 2 mg/5 mL; DEXTROMETHORPHAN HYDROBROMIDE 10 mg/5 mL
INACTIVE INGREDIENTS: CITRIC ACID; FD&C RED NO. 40; METHYLPARABEN; PROPYLPARABEN; SODIUM CITRATE; PROPYLENE GLYCOL; D&C RED NO. 33; WATER; SUCRALOSE

RYCONTUSS

ACTIVE INGREDIENT SECTION

CHLORPHENIRAMINE MALEATE 2MG

DEXTROMETHORPHAN HYDROBROMIDE 10MG

PHENYLEPHRINE HYDROCHLORIDE 5MG

INACTIVE INGREDIENT SECTION

CITRIC ACID, D&C RED#33, FD&C RED#40, NATURAL FLAVOR, METHYLPARABEN, PROPYLENE GLYCOL, PROPYLPARABEN, PURIFIED WATER, SODIUM CITRATE AND SUCRALOSE.

ASK A DOCTOR SECTION

aSK A DOCTOR OR PHARMACIST IF YOU ARE TAKINGSEDATIVES OR TRANKILIZERS.

DO NOT USE SECTION

DO NORT USE TO SEDATE A CHILD OR TO MAKE A CHILD SLEEPY.

Do not use if you are now taking a prescription monoamine oxidase inhibitor(MAOI) (certain drugs for depression, psychiatric or emotional condition, or for 2 weeks after stopping the MAOI drug. If you do not know if your prescription drug contains an MAOI ask a doctor or pharmacist before taking this product.

Keep out of reach of children section.

In case of a overdose, get medical help or contact a Poison Control Center right away.

Pregnancy or breast feeding section

If pregnancy or breaft-feeding, ask a heath professional before use

PURPOSE SECTION

ANTIHISTAMINE, COUGH SUPRESSANT AND NASAL DESCONGESTANT.

QUESTION SECTION

QUESTION OR COMMENTS:

PHONE 1-787-548-0016. LABOR HOUR 8:00 AM TO 5:00 PM.

STOP USE SECTION.

STOP USE OR ASK A DOCTOR IF:

YOU GET NERVOUS, DIZZY, OR SLEEPLESS

COUGH LAST MORE THAN 7 DAYS, COMES BACK, OR IS ACCOMPANIED BY FEVER, RASH OR PERSISTENT HEADACHES.

WARNINGS SECTION

DO NORT USE TO SEDATE A CHILD OR TO MAKE A CHILD SLEEPY.

Do not use if you are now taking a prescription monoamine oxidase inhibitor(MAOI) (certain drugs for depression, psychiatric or emotional condition, or for 2 weeks after stopping the MAOI drug. If you do not know if your prescription drug contains an MAOI ask a doctor or pharmacist before taking this product.

INDICATION AND USAGE

Uses for the temporary relief of runny nose, sneezing, itching of the nose or throat, and itchy, watery eyes due to hay fever.

Temporarily relieves cough due to minor throat and bronchial irritation occuring with comon cold.

Temporarily restore freer breathing through the nose.

Adults and children 12 or older--------2 tsp (10 ml) every 4 hours

Children age 6 - 12 ----- 1 tsp (5ml) every 4 hours

Children younger tahn 6. ------ Ask a doctor

Dosage and administration

Adults and children 12 or older--------2 tsp (10 ml) every 4 hours

Children age 6 - 12 ----- 1 tsp (5ml) every 4 hours

Children younger tahn 6. ------ Ask a doctor

Package Label-Principal Display Panel

NDC 76117 - 001 - 16

RYCONTUSS

LIQUID

CHERRY FLAVOR

ANTITISSIVE NASAL

DECONGESTANT AND

ANTIHISTAMINE

16 FL OZ (1 PINT) (473 ML)